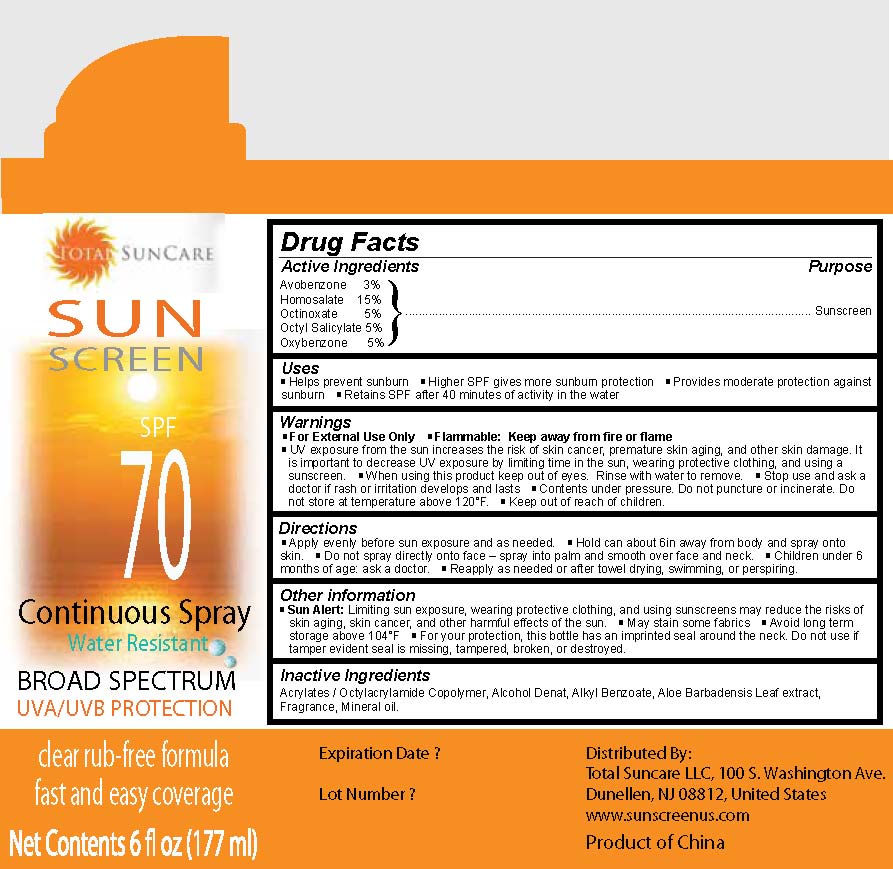 DRUG LABEL: Total Suncare Sunscreen SPF 70
NDC: 49893-500 | Form: SPRAY
Manufacturer: Total Suncare LLC
Category: otc | Type: HUMAN OTC DRUG LABEL
Date: 20091208

ACTIVE INGREDIENTS: AVOBENZONE 3 mL/100 mL; HOMOSALATE 15 mL/100 mL; OCTINOXATE 5 mL/100 mL; OCTISALATE 5 mL/100 mL; OXYBENZONE 5 mL/100 mL
INACTIVE INGREDIENTS: ALCOHOL; ALOE VERA LEAF; MINERAL OIL

Sunscreen SPF 70

Active Ingredients

Avobenzone 3 percent
Homosalate 15 percent
Octinoxate 5 percent
Octyl Salicylate 5 percent
Oxybenzone 5 percent

Purpose

Sunscreen

Uses
- Helps prevent sunburn
- Higher SPF gives more sunburn protection
- Provides moderate protection against sunburn
- Retains SPF after 40 minutes of activity in the water

Warnings
- For External Use Only
- Flammable: Keep away from fire or flame
- UV exposure from the sun increases the risk of skin cancer, premature skin aging,
and other skin damage. It is important to decrease UV exposure by limiting time in
the sun, wearing protective clothing, and using a sunscreen.
- When using this product keep out of eyes. Rinse with water to remove.
- Stop use and ask a doctor if rash or irritation develops and lasts
- Contents under pressure. Do not puncture or incinerate. Do not store at temperature
above 120 degrees F.
- Keep out of reach of children.

Directions
- Apply evenly before sun exposure and as needed.
- Hold can about 6in away from body and spray onto skin.
- Do not spray onto face - spray into palm and smooth over face and neck.
- Children under 6 months of age: ask a doctor.
- Reapply as needed or after towel drying, swimming, or perspiring.

Other Information
- Sun Alert: Limiting sun exposure, wearing protective clothing, and using sunscreens may
reduce the risks of skin aging, skin cancer, and other harmful effects of the sun.
- May stain some fabrics
- Avoid long term storage above 104 degrees F
- For your protection, this bottle has an imprinted seal around the neck. Do not use if
tamper evident seal is missing, tampered, broken, or destroyed.

INACTIVE INGREDIENT

Acrylates / Octylacrylamide Copolymer, Alcohol Denat, Alkyl Benzoate, Aloe Barbadensis Leaf extract, Fragrance, Mineral oil

PACKAGE LABEL

Total SunCare
SUN
SCREEN
SPF 70

Contininous Spray
Water Resistant

BROAD SPECTRUM
UVA/UVB PROTECTION

clear rub-free free formula
fast and easy coverage

Net Contents 6 fl oz (177 ml)

Expiration Date?
Lot Number?
Distributed By:
Total Suncare LLC, 100 S. Washington Ave.
Dunellen, NJ 08812, United States
www.sunscreenus.com
Product of China